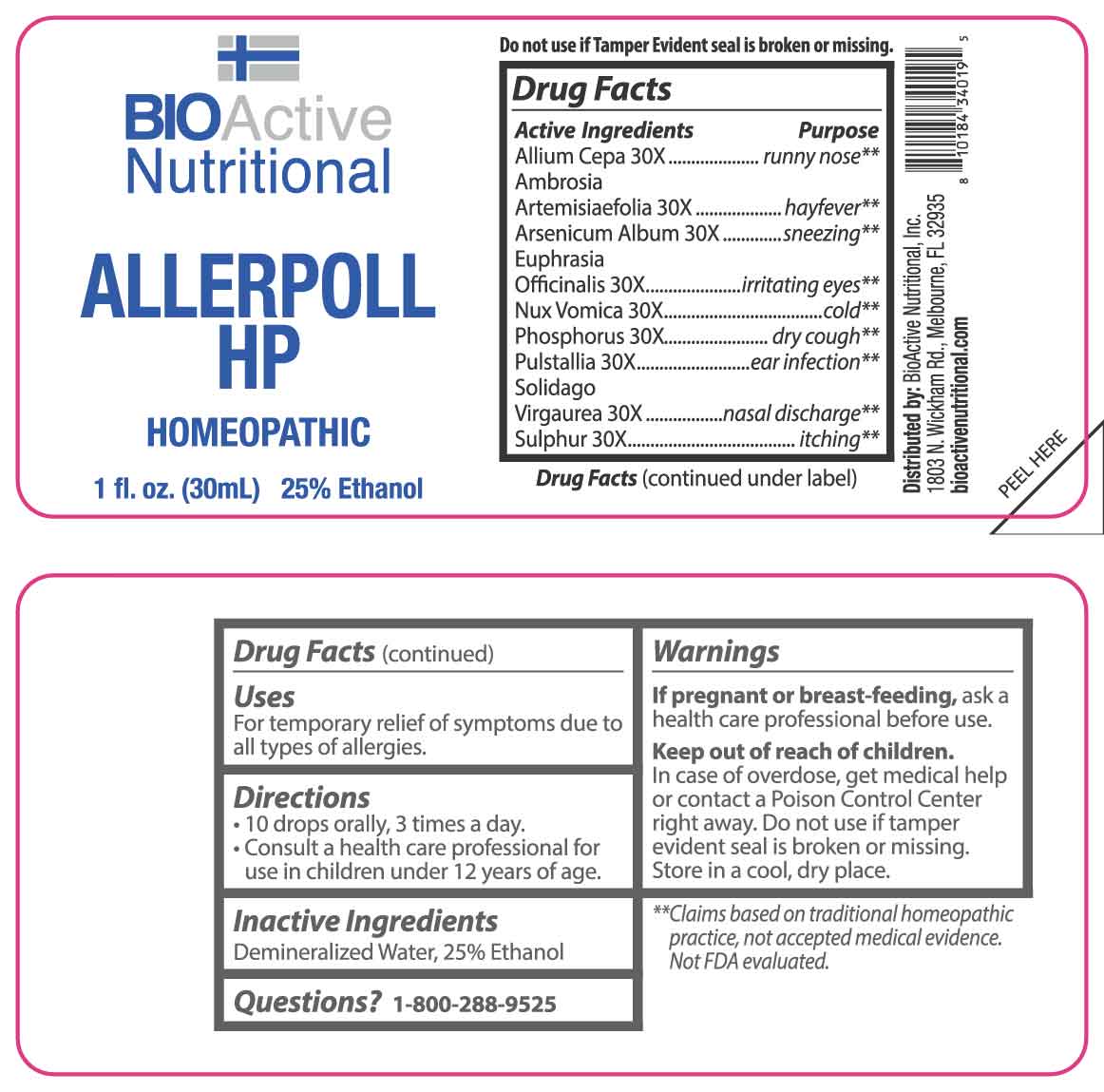 DRUG LABEL: Allerpoll
NDC: 43857-0058 | Form: LIQUID
Manufacturer: BioActive Nutritional, Inc.
Category: homeopathic | Type: HUMAN OTC DRUG LABEL
Date: 20250403

ACTIVE INGREDIENTS: ONION 30 [hp_X]/1 mL; AMBROSIA ARTEMISIIFOLIA WHOLE 30 [hp_X]/1 mL; ARSENIC TRIOXIDE 30 [hp_X]/1 mL; EUPHRASIA STRICTA 30 [hp_X]/1 mL; STRYCHNOS NUX-VOMICA SEED 30 [hp_X]/1 mL; PHOSPHORUS 30 [hp_X]/1 mL; PULSATILLA VULGARIS WHOLE 30 [hp_X]/1 mL; SOLIDAGO VIRGAUREA FLOWERING TOP 30 [hp_X]/1 mL; SULFUR 30 [hp_X]/1 mL
INACTIVE INGREDIENTS: Water; ALCOHOL

DRUG FACTS:

ACTIVE INGREDIENTS:

Allium Cepa 30X, Ambrosia Artemisiaefolia 30X, Arsenicum Album 30X, Euphrasia Officinalis 30X, Nux Vomica 30X, Phosphorus 30X, Pulsatilla 30X, Solidago Virgaurea 30X, Sulphur 30X.

PURPOSE:

Allium Cepa – runny nose,** Ambrosia Artemisiaefolia - hayfever,** Arsenicum Album - sneezing,** Euphrasia Officinalis – irritating eyes,** Nux Vomica - cold,** Phosphorus – dry cough,** Pulsatilla – ear infection,** Solidago Virgaurea – nasal discharge,** Sulphur – itching**
**Claims based on traditional homeopathic practice, not accepted medical evidence. Not FDA Evaluated.

USES:

For temporary relief of symptoms due to all types of allergies.

WARNINGS:

If pregnant or breast-feeding, ask a health care professional before use.

Keep out of reach of children. In case of overdose, get medical help or contact a Poison Control Center right away.

Do not use if tamper evident seal is broken or missing.

Store in a cool, dry place.

KEEP OUT OF REACH OF CHILDREN:

In case of overdose, get medical help or contact a Poison Control Center right away.

DIRECTIONS:

• 10 drops orally, 3 times a day.

• Consult a health care professional for use in children under 12 years of age.

INACTIVE INGREDIENTS:

Demineralized Water, 25% Ethanol

QUESTIONS:

Distributed by:
BioActive Nutritional, Inc.
1803 N. Wickham Rd.
Melbourne, FL 32935
bioactivenutritional.com

1-800-288-9525

PACKAGE LABEL DISPLAY:

BIOActive Nutritional

ALLERPOLL HP

HOMEOPATHIC

1 FL OZ (30 ml)